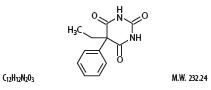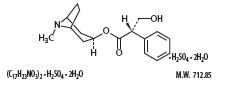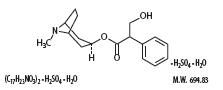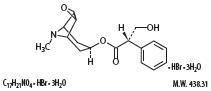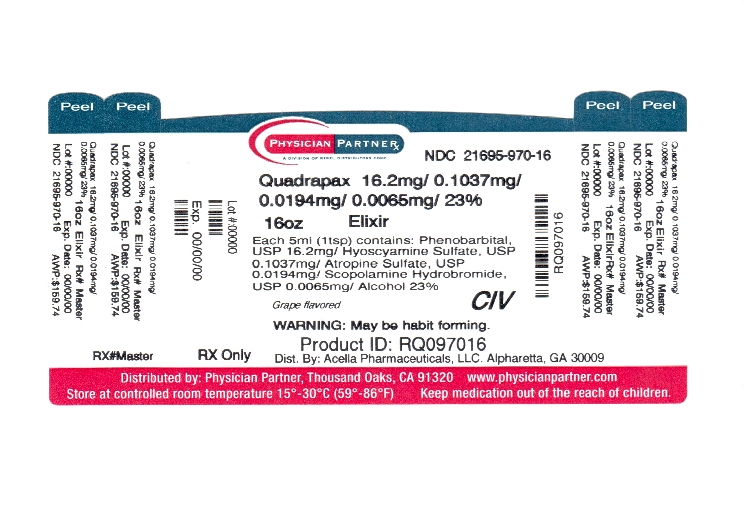 DRUG LABEL: QUADRAPAX
NDC: 21695-970 | Form: ELIXIR
Manufacturer: Rebel Distributors Corp
Category: prescription | Type: HUMAN PRESCRIPTION DRUG LABEL
Date: 20110913
DEA Schedule: CIV

ACTIVE INGREDIENTS: Phenobarbital 16.2 mg/5 mL; Hyoscyamine Sulfate 0.1037 mg/5 mL; Atropine Sulfate 0.0194 mg/5 mL; Scopolamine Hydrobromide 0.0065 mg/5 mL
INACTIVE INGREDIENTS: Alcohol; Glycerin; Water; Saccharin Sodium; Sorbitol; Sucrose

QUADRAPAX ELIXIR

DESCRIPTION:

Each 5 mL (one teaspoonful) for oral administration contains:

Phenobarbital, USP.......................................................16.2 mg

(WARNING: May be habit forming)

Hyoscyamine sulfate, USP.........................................0.1037 mg

Atropine sulfate, USP.................................................0.0194 mg

Scopolamine hydrobromide, USP................................0.0065 mg

Alcohol...............................................................................23%

INACTIVE INGREDIENTS:

Artificial grape flavor, ethyl alcohol, FD and C blue #1, FD and C red #40, glycerin, purified water USP, sodium saccharin, sorbitol solution 70%, and sucrose.

Phenobarbital is a barbiturate with the chemical name 5-Ethyl-5-phenylbarbituric acid. It has the following structural formula:

Hyoscyamine sulfate is a belladonna alkaloid with the chemical name Benzeneacetic acid, α-(hydroxmethyl)-, 8-methyl-8-azabicyclo[3.2.1]oct-3-yl ester, [3(S)-endo]-,sulfate (2:1), dihydrate. It has the following structural formula:

Atropine sulfate is belladonna alkaloid with the chemical name: Benzeneacetic acid, α-(hydroxymethyl)-, 8-methyl-8-azabicyclo[3.2.1]oct-3-yl ester, endo (±)-, sulfate (2:1) (salt), monohydrate. It has the following structural formula:

Scopolamine is a belladonna alkaloid with the chemical name Benezeneacetic acid, α-(hydroxymethyl)-, 9-methyl-3-oxa-9-azatricyclo[3.31.0.^2,4]non-[7-yl ester, hydrobromide, rihydrate, [7(S)-(1α,2β,4β,5α,7β)]-. It has the following structural formula:

CLINICAL PHARMACOLOGY:

Phenobarbital is a barbiturate, nonselective central nervous system depressant which is primarily used as a sedative hypnotic and also as an anticonvulsant in subhypnotic doses. Atropine Sulfate, Hyoscyamine Sulfate and Scopolamine Hydrobromide are belladonna alkaloids classified as anticholinergic, antimuscarinic drugs and act to inhibit muscarinic actions of acetycholine at postganglionic parasympathetic neuron effector sites. These drugs are also used as antispasmodics due to their anticholinergic action and produce the effect in the body of reduced muscle spasms in the digestive or urinary tract, and reduced fluid secretions from certain glands or organs. This drug combination provides peripheral anticholinergic/antispasmodic action and mild sedation.

INDICATIONS AND USAGE:

FDA has classified the following indications as "possibly" effective: For use as adjunctive therapy in the treatment of irritable bowel syndrome (irritable colon, spastic colon, mucous colitis) and acute enterocolitis. May also be useful as adjunctive therapy in the treatment of duodenal ulcer.

IT HAS NOT BEEN SHOWN CONCLUSIVELY WHETHER ANTICHOLINERGIC/ANTISPASMODIC DRUGS AID IN THE HEALING OF A DUODENAL ULCER, DECREASE THE RATE OF RECURRENCES OR PREVENT COMPLICATIONS.

CONTRAINDICATIONS:

Quadrapax Elixir is contraindicated in patients with known hypersensitivity to any of the ingredients. Phenobarbital is contraindicated in patients with acute intermittent porphyria and in those patients in which phenobarbital produces restlessness and/or excitement.

It is also contraindicated in patients with glaucoma, obstructive uropathy; paralytic ileus; myasthenia gravis; intestinal atony; unstable cardiovascular status in acute hemorrhage; hiatal hernia associated with reflux esophagitis; obstructive disease of the gastrointestinal tract; or severe ulcerative colitis.

WARNINGS:

Heat prostration can occur with belladonna alkaloids in high temperatures.

Diarrhea may be an early symptom of incomplete intestinal obstruction, especially in patients with ileostomy or colostomy. In this instance, treatment with this drug could be harmful.

Quadrapax Elixir

may produce drowsiness and blurred vision. The patient should be warned about engaging in hazardous work or activities requiring mental alertness, such as operating a motor vehicle or other machinery. Phenobarbital may decrease the effect of anticoagulants, and larger doses of the anticoagulant may be needed for optimal effect. When phenobarbital is discontinued, the dose of the anticoagulant may have to be decreased. Phenobarbital may be habit forming and should not be administered to patients who are susceptible to addiction or to those with a history of physical and/or psychological drug dependence.

Barbiturates should be used with caution in patients with hepatic dysfunction.

PRECAUTIONS:

GENERAL:

Use with caution in patients with prostatic hypertrophy, autonomic neuropathy, hepatic or renal disease, hyperthyroidism, coronary heart disease, congestive heart failure, cardiac arrhythmias, tachycardia, and hypertension.

Belladonna alkaloids may produce a delay in gastric emptying (antral stasis) which would complicate the management of gastric ulcer. Do not rely on the use of the drug in the presence of complication of biliary tract disease. Theoretically, with overdosage, a curare-like action may occur.

INFORMATION FOR PATIENTS:

Practitioners should give the following information and instructions to patients:

- Do not increase the dose of this drug without consulting a physician.
- Do not share this medication with others.

The use of this product caries with it an associated risk of psychological and/or physical dependence.

The use of this product may impair mental and/or physical abilities required for the performance of potentially hazardous tasks such as driving or operating machinery.

Use of this product with alcohol may result in additional central nervous system depressant effects.

Tell your doctor or pharmacist if you also take antihistamines, anti-seizure drugs, medicine for sleep or anxiety, muscle relaxants, narcotic pain relievers, or psychiatric medicines.

This drug may increase the risk for heatstroke because it decreases sweating. Avoid becoming overheated in hot weather, saunas, and during exercise or other strenuous activity.

DRUG INTERACTIONS:

Do not take this medicine with the following medications:

- voriconazole
- pramlintide.

This medicine may also interact with the following medication:

CNS depressants

cyclosporine

female hormones, like estrogens or progestins and birth control pills

medicines for HIV infection like indinavir, nelfinavir, ritonavir, and saquinavir

warfarin

amantadine

anti-Parkinson's drugs levodopa, benztropine, trihexphenidyl

antispasmodic drugs clidinium, dicyclomine, propantheline

MAO inhibitors furazolidone, isocarboxazid, linezolid, moclobemide, phenelzine, procarbazine, rasagiline, selegiline, tranylcpromine

anti-arrhythmic drugs disopyramide, procainamide, quinidine

azole anti-fungal drugs ketoconazole, itraconzole

bisphosphonate drugs alendronate, risedronate

corticosteroid prednisone

digoxin (slow-dissolving tablets)

phenothiazines (Promethazine)

potassium tablets/capsules

anti-seizure drug carbamazepine

anti-anxiety drugs alprazolam, diazepam, zolpidem

narcotic pain relievers

psychiatric drugs chlorpromazine, haloperidol, amitriptyline,risperidone

certain antihistamines diphenhydramine, meclizine

muscle relaxants

CARCINOGENESIS, MUTAGENESIS, IMPAIRMENT OF FERTILITY:

Long-term studies in animals have not been performed to evaluate carcinogenic potential.

PREGNANCY TERATOGENIC EFFECTS:

Pregnancy Category D.

Quadrapax Elixir

can cause fetal harm when administered to a pregnant woman. Retrospective case-controlled studies have suggested a connection between the maternal consumption of phenobarbital and higher than expected incidence of fetal abnormalities. Following oral administration, phenobarbital readily crosses the placental barrier and is distributed throughout fetal tissues with highest concentrations found in the placenta, fetal liver, and brain. If this drug is used during pregnancy, or if the patient becomes pregnant while taking this drug, the patient should be apprised of the potential hazard to the fetus.

NONTERATOGENIC EFFECTS:

Reports of infants suffering from long-term phenobarbital exposure in utero included the acute withdrawal syndrome of seizures and hyperirritability from birth to a delayed onset of up to 14 days.

LABOR AND DELIVERY:

Administration of

Quadrapax Elixir

to the mother during labor may result in respiratory depression in the newborn. Premature infants are particularly susceptible to the depressant effects.

NURSING MOTHERS:

Caution should be exercised when

Quadrapax Elixir

is administered to a nursing woman. The active ingredients contained in this drug product are known to be excreted in human milk.

SPECIAL PATIENT POPULATION:

Dosage should be reduces in the debilitated because these patients may be more sensitive to phenobarbital. Dosage should be reduced for patients with impaired renal function or hepatic disease.

PEDIATRIC USE:

Use

Quadrapax Elixir

with caution in children as they may be more susceptible to the effects of this product especially infants, children with Down's syndrome, spastic paralysis or brain damage.

GERIATRIC USE:

Sedating drugs may cause confusion and over-sedation in the elderly; elderly patients generally should be started on low doses of

Quadrapax Elixir

and observed closely. This drug is known to be substantially excreted by the kidney, and the risk of toxic reactions to this drug may be greater in patients with impaired renal function. Because elderly patients are more likely to have decreased renal function, care should be taken in dose selection, and it may be useful to monitor renal function.

ADVERSE REACTIONS:

Adverse reactions associated with anticholinergics and/or anticonvulsants are: dry mouth; tachycardia; urinary hesitancy and retention; palpitation; blurred vision; prolonged pupil dilation; cycloplegia; increased ocular tension; loss of taste sense; headache; nervousness; drowsiness; weakness; dizziness; insomnia; nausea; vomiting; severe allergic reaction or drug idiosyncrasies, including anaphylaxis, hives and/or other dermal manifestations; decreased sweating; impotence; suppression of lactation; constipation; bloated feeling and musculoskeletal pain. Elderly patients may react with symptoms of excitement, agitation and drowsiness to even small doses of the drug. Phenobarbital may produce excitement in some patients, rather than a sedative effect. In patients habituated to barbiturates, abrupt withdrawal may produce delirium or convulsions.

DRUG ABUSE AND DEPENDENCE:

This product is subject to the provisions of the Controlled Substance Act and has been placed in Schedule IV. Phenobarbital may be habit-forming. Tolerance, psychological dependence, and physical dependence may occur following prolonged use.

Call your doctor for medical advice about side effects. You may report side effects to the FDA at 1-800-FDA-1088.

OVERDOSAGE

An overdose of

Quadrapax Elixir

is a potentially lethal overdose situation. Call your doctor or a Poison Control Center immediately if an overdose is suspected.

SIGNS AND SYMPTOMS:

Characteristics of phenobarbital overdose include decreased consciousness leading to coma, bradycardia, bradypnea, hypothermia and hypotention. Overdose may also lead to pulmonary edema and acute renal failure as result of shock. Other symptoms of an overdose with this product include headache, nausea, vomiting, tachycardia, severe or persistent blurred vision, dilated pupils, hot and dry skin, dizziness or disorientation, severe dryness of the mouth, difficulty in swallowing, and CNS stimulation.

RECOMMENDED TREATMENT:

Treatment of overdose is supportive, and consists mainly in the maintenance of airway patency through endotracheal intubation and mechanical ventilation, correction of bradycardia and hypotention with intravenous fluids and vasopressors, if necessary, and removal of as much drug as possible from the body. Depending on how much time has elapsed since ingestion of the drug, this may be accomplished through gastric lavage or use of activated charcoal.

DOSAGE AND ADMINISTRATION:

The dosage of

Quadrapax Elixir

should be adjusted to the needs of the individual patient to assure symptomatic control with a minimum of adverse effects.

Adults:

One or two teaspoonfuls of elixir three to four times a day according to conditions and severity of symptoms.

Pediatric patients:

may be dosed every 4 to 6 hours.

Starting dosage

Body weight | q4h | q6h
10 lb. (4.5 kg) | 0.5 mL | 0.75 mL
20 lb. (9.1 kg) | 1.0 mL | 1.5 mL
30 lb. (13.6 kg) | 1.5 mL | 2.0 mL
50 lb. (22.7 kg) | 1/2 tsp | 3/4 tsp
75 lb. (34 kg) | 3/4 tsp | 1 tsp
100 lb. (45.4 kg) | 1 tsp | 1 1/2 tsp

Children under 2 years of age:

as directed by a physician.

HOW SUPPLIED:

Quadrapax Elixir is a purple colored, grape flavored liquid.

1 Pint (16 fl oz.) bottles NDC 21695-970-16.

Store at 20°- 25°C(68°- 77°F) [see USP Controlled Room Temperature].

Excursions permitted to 15°- 30°C(59°- 86°F).

Tamper evident by foil seal under cap. Do not use if foil seal is broken or missing.

WARNINGS: KEEP THIS AND ALL DRUGS OUT OF THE REACH OF CHILDREN. IN CASE OF ACCIDENTAL OVERDOSE, SEEK PROFESSIONAL ASSISTANCE OR CONTACT A POISON CONTROL CENTER IMMEDIATELY.

Manufactured for:

Acella PHARMACEUTICALS, LLC

Acella Pharmaceuticals, LLC

Alpharetta, GA 30009

Iss. 03/11

Relabeled by:

Rebel Distributors Corp

Thousand Oaks, CA 91320

PRODUCT PACKAGING:

The packaging below represents the labeling currently used:

Principal display panel and side panel for 473 mL label:

NDC 21695-970-16
QUADRAPAX ELIXIR

Grape Flavored

Each 5 mL (one teaspoonful) for oral administration contains:

Phenobarbital, USP.................................................16.2 mg

(WARNING: may be habit forming)

Hyoscyamine sulfate, USP...................................0.1037 mg

Atropine sulfate, USP...........................................0.0194 mg

Scopolamine hydrobromide, USP..........................0.0065 mg

Alcohol........................................................................23%

CIV
Bulk Container
Not For Household Use
Rx ONLY
1 Pint
(16 fl oz / 473 mL)

Acella PHARMACEUTICALS, LLC

Tamper evident by foil seal under cap. Do not use if foil seal is broken or missing.

THIS BOTTLE IS NOT TO BE DISPENSED TO THE CONSUMER.
WARNINGS: KEEP THIS AND ALL DRUGS OUT OF THE REACH OF CHILDREN. IN CASE OF ACCIDENTAL OVERDOSE,
SEEK PROFESSIONAL ASSISTANCE OR CONTACT A POISON CONTROL CENTER IMMEDIATELY.

May be habit forming.

Store at 20°- 25°C (68°- 77°F) [see USP Controlled Room Temperature].

Excursions permitted to 15°- 30°C (59°- 86°F).

Avoid freezing.

Protect from light.

Dispense in a tight, light-resistant cap.

Manufactured for:

Acella Pharmaceuticals, LLC

Alpharetta, GA 30009

Iss. 03/11

Relabeled by:

Rebel Distributors Corp

Thousand Oaks, CA 91320